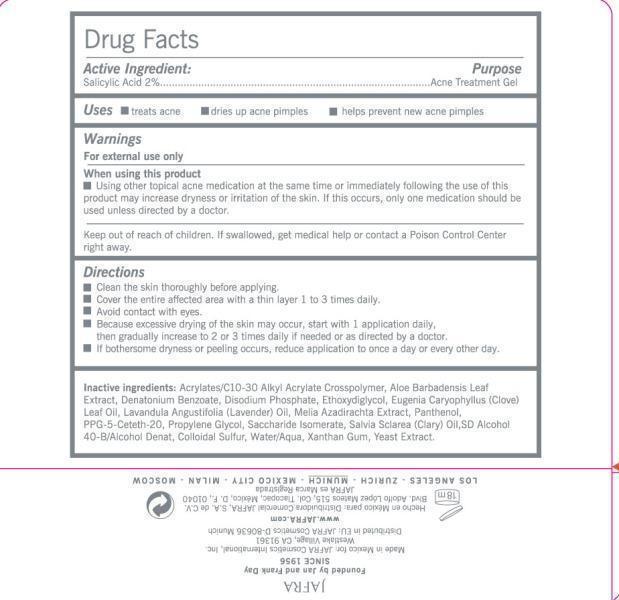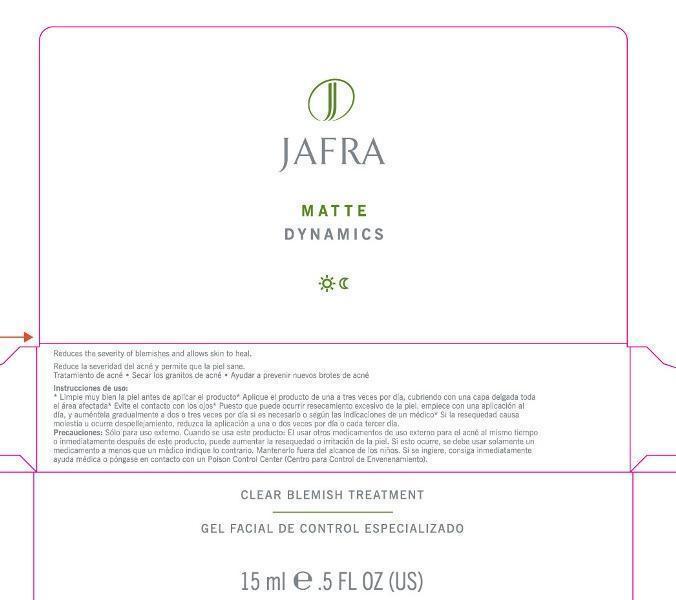 DRUG LABEL: Clear Blemish Treatment

NDC: 68828-129 | Form: GEL
Manufacturer: JAFRA COSMETICS INTERNATIONAL
Category: otc | Type: HUMAN OTC DRUG LABEL
Date: 20200622

ACTIVE INGREDIENTS: SALICYLIC ACID 2 g/151 mL
INACTIVE INGREDIENTS: CARBOMER COPOLYMER TYPE A (ALLYL PENTAERYTHRITOL CROSSLINKED); ALOE VERA LEAF; DENATONIUM BENZOATE; SODIUM PHOSPHATE, DIBASIC, ANHYDROUS; DIETHYLENE GLYCOL MONOETHYL ETHER; CLOVE LEAF OIL; LAVENDER OIL; AZADIRACHTA INDICA BARK; PANTHENOL; PPG-5-CETETH-20; PROPYLENE GLYCOL; SACCHARIDE ISOMERATE; CLARY SAGE OIL; XANTHAN GUM; YEAST

Clear Blemish Treatment

Active ingredient Purpose

Salicylic Acid 2% Acne treatment Gel

Uses

treats acne

dries up acne pimples

helps prevent new acne pimples

Keep out of reach of children. If swallowed, get medical help or contact a Poison Control Center right away.

When using this product

using other topical acne medication at the same time or immediately following the use of this product may increase dryness or irritation of the skin. If this occurs, only one medication should be used unless directed by a doctor.

Warnings

For external use only

Directions

Clean the skin thoroughly before applying.

Cover the entire affected area with a thin layer 1 to 3 times daily.

Avoid contact with eyes

Because excessive drying of the skin may occur start with 1 application daily, then gradually increase to 2 or 3 times daily.

If bothersome dryness or peeling occurs, reduce application to once a day or every other day.

INACTIVE INGREDIENT

Inactive Ingredients: Acrylates/C10-30 Alkyl acrylate Crosspolymer, Aloe Barbadensis Leaf Extract, Denatonium Benzoate, Disodium Phosphate, Ethoxydiglycol, Eugenia Caryophyllus (clove) Leaf Oil, Lavandula Angustifolia (Lavender) Oil, Melia Azadirachta Extract, Panthenol, PPG-5 Ceteth-20, Propylene Glycol, Saccharide Isomerate, Salvia Sclarea (Clary) Oil, SD Alcohol 40-B/Alcohol Denat, Colloidal Sulfur, Water/Aqua, Xanthan Gum, Yeast Extract.

PACKAGE LABEL

Clear Blemish Treatment

Gel Facial De Control Expecializado

15 ml .5 Fl Oz US